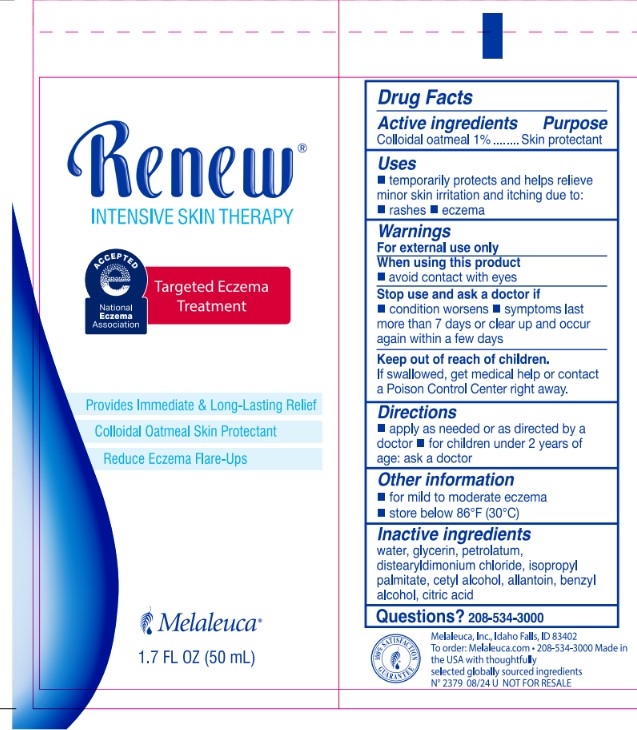 DRUG LABEL: Renew Intensive Skin Therapy
NDC: 54473-410 | Form: CREAM
Manufacturer: Melaleuca Inc.
Category: otc | Type: HUMAN OTC DRUG LABEL
Date: 20251031

ACTIVE INGREDIENTS: OATMEAL 0.5 g/50 mL
INACTIVE INGREDIENTS: PETROLATUM; ISOPROPYL PALMITATE; ALLANTOIN; DISTEARYLDIMONIUM CHLORIDE; GLYCERIN; CETYL ALCOHOL; WATER; BENZYL ALCOHOL; CITRIC ACID MONOHYDRATE

Renew Targeted Eczema Treatment

Active Ingredients

Colloidal oatmeal 1%

Purpose

Skin protectant

INDICATIONS AND USAGE

Uses Temporarily protects and helps relieve minor skin irritation and itching due to:

- rashes
- eczema

Warnings

For external use only

When using this product avoid contact with eyes

Stop use and ask a doctor if

- Condition worsens
- symptoms last more than 7 days or clear up and occur again within a few days

Keep out of reach of children. If swallowed, get medical help or contact a Poison Control Center right away.

Directions

- apply as needed or as directed by a doctor
- for children under 2 years of age: ask a doctor

Other information

- for mild to moderate eczema
- store below 86 F (30 C)

INACTIVE INGREDIENT

water, glycerin, petrolatum, distearyldimonium chloride, isopropyl palmitate, cetyl alcohol, allantoin, benzyl alcohol, citric acid